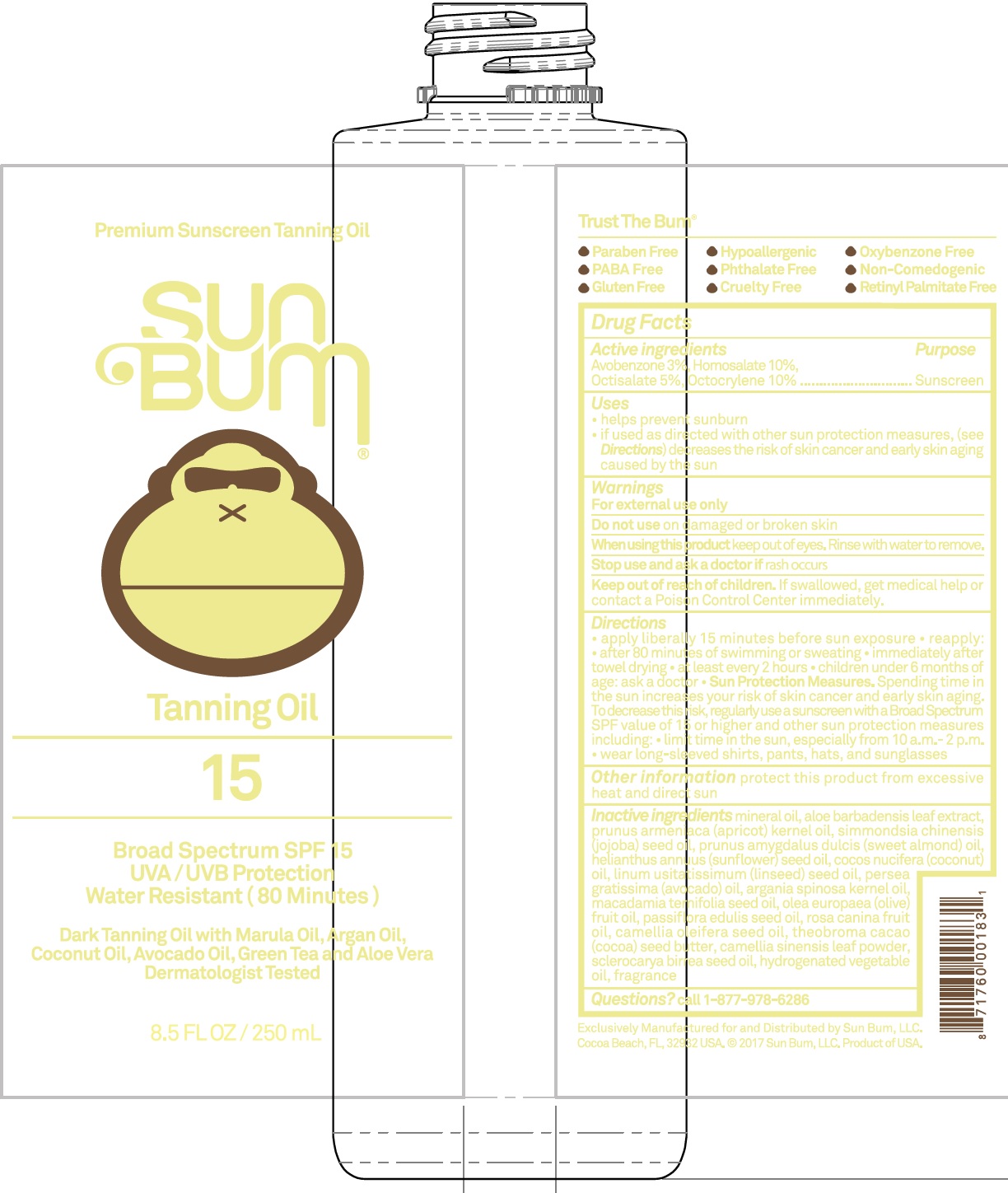 DRUG LABEL: Sun Bum Premium SPF 15 Sunscreen Tanning
NDC: 69039-278 | Form: OIL
Manufacturer: Sun Bum LLC
Category: otc | Type: HUMAN OTC DRUG LABEL
Date: 20220204

ACTIVE INGREDIENTS: AVOBENZONE 30 mg/1 mL; HOMOSALATE 100 mg/1 mL; OCTISALATE 50 mg/1 mL; OCTOCRYLENE 100 mg/1 mL
INACTIVE INGREDIENTS: MINERAL OIL; ALOE VERA LEAF; APRICOT KERNEL OIL; JOJOBA OIL; ALMOND OIL; SUNFLOWER OIL; COCONUT OIL; LINSEED OIL; AVOCADO OIL; ARGAN OIL; MACADAMIA OIL; OLIVE OIL; PASSIFLORA EDULIS SEED OIL; ROSA CANINA FRUIT OIL; CAMELLIA OIL; COCOA BUTTER; GREEN TEA LEAF; SCLEROCARYA BIRREA SEED OIL

Sun Bum Premium SPF 15 Sunscreen Tanning Oil

Active Ingredients

Avobenzone 3%, Homosalate 10%,

Octisalate 5% Octocrylene 10%

Purpose

Sunscreen

Uses

- helps prevent sunburn
- if used as directed with other sun protection measures, (see Directions) decreases the risk of skin cancer and early skin aging caused by the sun

Warnings

For external use only

Do not use

on damaged or broken skin

When using this product:

keep out of eyes. Rinse with water to remove.

Stop use and ask a doctor

if rash occurs

Keep out of reach of children.

If swallowed, get medical help or contact a Poison Control Center immediately.

Directions

• apply liberally 15 minutes before sun exposure • reapply: • after 80 minutes of swimming or sweating • immediately after towel drying • at least every 2 hours • children under 6 months of age: ask a doctor • Sun Protection Measures. Spending time in the sun increases your risk of skin cancer and early skin aging. To decrease this risk, regularly use a sunscreen with a Broad Spectrum SPF of 15 or higher and other sun protection measures, including: • limit time in the sun, especially from 10 a.m. - 2 p.m. • wear long-sleeved shirts, pants, hats, and sunglasses

Other Information

protect this product from excessive heat and direct sun

Inactive ingredients

mineral oil, aloe barbadensis leaf extract, prunus armeniaca (apricot) kernel oil, simmondsia chinensis (jojoba) seed oil, prunus amygdalus dulcis (sweet almond) oil, helianthus annuus (sunflower) seed oil, cocos nucifera (coconut) oil, linum usitatissimum (linseed) seed oil, persea gratissima (avocado) oil, argania spinosa kernel oil, macadamia ternifolia seed oil, olea europaea (olive) fruit oil, passiflora edulis seed oil, rosa canina fruit oil, camellia oleifera seed oil, theobroma cacao (cocoa) seed butter, camellia sinensis leaf powder, sclerocarya birrea seed oil, hydrogenated vegetable oil, fragrance

Questions?

Call 1-877-978-6286